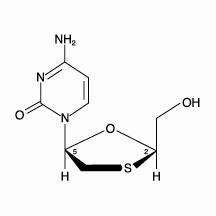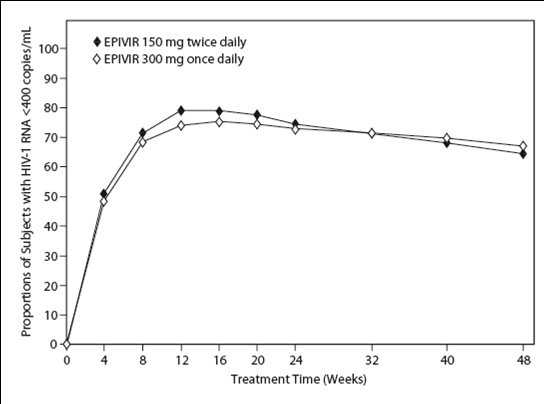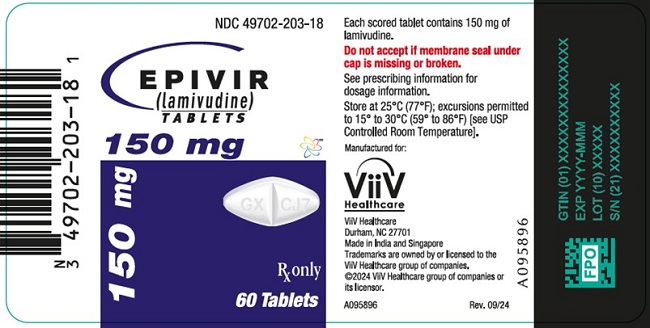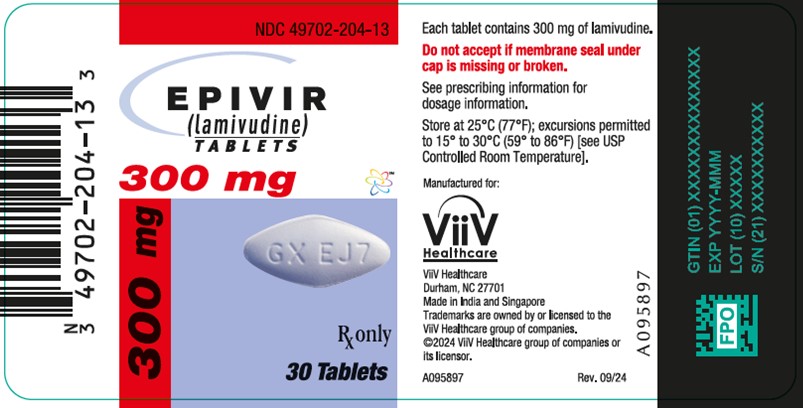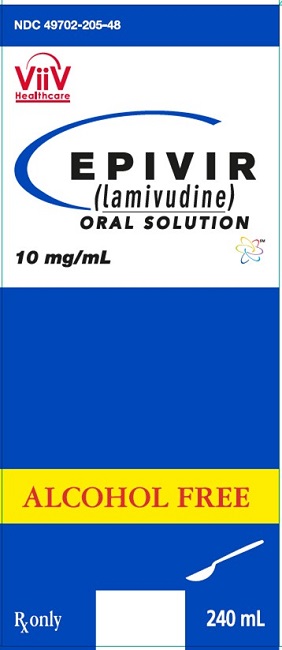 DRUG LABEL: EPIVIR
NDC: 49702-203 | Form: TABLET, FILM COATED
Manufacturer: ViiV Healthcare Company
Category: prescription | Type: HUMAN PRESCRIPTION DRUG LABEL
Date: 20240815

ACTIVE INGREDIENTS: LAMIVUDINE 150 mg/1 1
INACTIVE INGREDIENTS: HYPROMELLOSE, UNSPECIFIED; MAGNESIUM STEARATE; MICROCRYSTALLINE CELLULOSE; POLYETHYLENE GLYCOL, UNSPECIFIED; POLYSORBATE 80; SODIUM STARCH GLYCOLATE TYPE A POTATO; TITANIUM DIOXIDE

HIGHLIGHTS OF PRESCRIBING INFORMATION

These highlights do not include all the information needed to use EPIVIR safely and effectively. See full prescribing information for EPIVIR.
EPIVIR (lamivudine) tablets, for oral use
EPIVIR (lamivudine) oral solution
Initial U.S. Approval: 1995

WARNING: EXACERBATIONS OF HEPATITIS B and DIFFERENT FORMULATIONS OF EPIVIR

See full prescribing information for complete boxed warning

- Severe acute exacerbations of hepatitis B have been reported in patients who are co-infected with hepatitis B virus (HBV) and human immunodeficiency virus (HIV-1) and have discontinued EPIVIR. Monitor hepatic function closely in these patients and, if appropriate, initiate anti-hepatitis B treatment. (5.1)
- Patients with HIV-1 infection should receive only dosage forms of EPIVIR appropriate for treatment of HIV-1. (5.1)

1 INDICATIONS AND USAGE

EPIVIR is a nucleoside analogue reverse transcriptase inhibitor indicated in combination with other antiretroviral agents for the treatment of HIV‑1 infection.
Limitations of Use: The dosage of this product is for HIV‑1 and not for HBV. (1)

2 DOSAGE AND ADMINISTRATION

- Adults: 300 mg daily, administered as either 150 mg twice daily or 300 mg once daily. (2.1)
- Pediatric Patients Aged 3 Months and Older: Administered either once or twice daily. Dose should be calculated on body weight (kg) and should not exceed 300 mg daily. (2.2)
- Patients with Renal Impairment: Doses of EPIVIR must be adjusted in accordance with renal function. (2.3)

3 DOSAGE FORMS AND STRENGTHS

- Tablets: 150 mg, scored (3)
- Tablets: 300 mg (3)
- Oral Solution: 10 mg per mL (3)

4 CONTRAINDICATIONS

EPIVIR is contraindicated in patients with previous hypersensitivity reaction to lamivudine. (4)

5 WARNINGS AND PRECAUTIONS

- Co-infected HIV‑1/HBV Patients: Emergence of lamivudine-resistant HBV variants associated with lamivudine‑containing antiretroviral regimens has been reported. (5.1)
- Lactic acidosis and severe hepatomegaly with steatosis, including fatal cases, have been reported with the use of nucleoside analogues. (5.2)
- Pancreatitis: Use with caution in pediatric patients with a history of pancreatitis or other significant risk factors for pancreatitis. Discontinue treatment as clinically appropriate. (5.3)
- Immune reconstitution syndrome has been reported in patients treated with combination antiretroviral therapy. (5.4)
- Lower virologic suppression rates and increased risk of viral resistance were observed in pediatric subjects who received EPIVIR oral solution concomitantly with other antiretroviral oral solutions compared with those who received tablets. An all-tablet regimen should be used when possible. (5.5)

6 ADVERSE REACTIONS

- The most common reported adverse reactions (incidence greater than or equal to 15%) in adults were headache, nausea, malaise and fatigue, nasal signs and symptoms, diarrhea, and cough. (6.1)
- The most common reported adverse reactions (incidence greater than or equal to 15%) in pediatric subjects were fever and cough. (6.1)

To report SUSPECTED ADVERSE REACTIONS, contact ViiV Healthcare at 1-877-844-8872 or FDA at 1-800-FDA-1088 or www.fda.gov/medwatch.

7 DRUG INTERACTIONS

Sorbitol: Coadministration of lamivudine and sorbitol may decrease lamivudine concentrations; when possible, avoid chronic coadministration. (7.2)

8 USE IN SPECIFIC POPULATIONS

- Lactation: Women infected with HIV should be instructed not to breastfeed due to potential for HIV transmission. (8.2)

FULL PRESCRIBING INFORMATION

WARNING: EXACERBATIONS OF HEPATITIS B and DIFFERENT FORMULATIONS OF EPIVIR

Exacerbations of Hepatitis B

Severe acute exacerbations of hepatitis B have been reported in patients who are co-infected with hepatitis B virus (HBV) and human immunodeficiency virus (HIV-1) and have discontinued EPIVIR. Hepatic function should be monitored closely with both clinical and laboratory follow-up for at least several months in patients who discontinue EPIVIR and are co-infected with HIV-1 and HBV. If appropriate, initiation of anti-hepatitis B therapy may be warranted [see Warnings and Precautions (5.1)].

Important Differences among Lamivudine-Containing Products

EPIVIR tablets and oral solution (used to treat HIV-1 infection) contain a higher dose of the active ingredient (lamivudine) than EPIVIR-HBV tablets and oral solution (used to treat chronic HBV infection). Patients with HIV-1 infection should receive only dosage forms appropriate for treatment of HIV-1 [see Warnings and Precautions (5.1)].

1 INDICATIONS AND USAGE

EPIVIR is a nucleoside analogue indicated in combination with other antiretroviral agents for the treatment of human immunodeficiency virus type 1 (HIV‑1) infection.

Limitations of Use:

- The dosage of this product is for HIV‑1 and not for HBV.

2 DOSAGE AND ADMINISTRATION

2.1 Recommended Dosage for Adult Patients

The recommended dosage of EPIVIR in HIV-1–infected adults is 300 mg daily, administered as either 150 mg taken orally twice daily or 300 mg taken orally once daily with or without food. If lamivudine is administered to a patient infected with HIV‑1 and HBV, the dosage indicated for HIV‑1 therapy should be used as part of an appropriate combination regimen [see Warnings and Precautions (5.1)].

2.2 Recommended Dosage for Pediatric Patients

EPIVIR scored tablet is the preferred formulation for HIV-1–infected pediatric patients who weigh at least 14 kg and for whom a solid dosage form is appropriate. Before prescribing EPIVIR scored tablets, pediatric patients should be assessed for the ability to swallow tablets. For patients unable to safely and reliably swallow EPIVIR tablets, the oral solution formulation may be prescribed [see Warnings and Precautions (5.5)]. The recommended oral dosage of EPIVIR tablets for HIV-1–infected pediatric patients is presented in Table 1.

Table 1. Dosing Recommendations for EPIVIR Scored (150-mg) Tablets in Pediatric Patients
Weight; (kg) | Once-Daily Dosing Regimena | Twice-Daily Dosing Regimen Using Scored 150-mg Tablet
Weight; (kg) | Once-Daily Dosing Regimena | AM Dose | PM Dose | Total Daily Dose
14 to <20 | 1 tablet (150 mg) | ½ tablet (75 mg) | ½ tablet (75 mg) | 150 mg
≥20 to <25 | 1½ tablets (225 mg) | ½ tablet (75 mg) | 1 tablet (150 mg) | 225 mg
≥25 | 2 tablets (300 mg)b | 1 tablet (150 mg) | 1 tablet (150 mg) | 300 mg
a Data regarding the efficacy of once-daily dosing is limited to subjects who transitioned from twice-daily dosing to once-daily dosing after 36 weeks of treatment [see Clinical Studies (14.2)].
b Patients may alternatively take one 300-mg tablet, which is not scored.

Oral Solution

The recommended dosage of EPIVIR oral solution in HIV-1–infected pediatric patients aged 3 months and older is 5 mg per kg taken orally twice daily or 10 mg per kg taken orally once daily (up to a maximum of 300 mg daily), administered in combination with other antiretroviral agents [see Clinical Pharmacology (12.3)]. Consider HIV-1 viral load and CD4+ cell count/percentage when selecting the dosing interval for patients initiating treatment with oral solution [see Warnings and Precautions (5.5), Clinical Pharmacology (12.3)].

2.3 Patients with Renal Impairment

Dosing of EPIVIR is adjusted in accordance with renal function. Dosage adjustments are listed in Table 2 [see Clinical Pharmacology (12.3)].

Table 2. Adjustment of Dosage of EPIVIR in Adults and Adolescents (Greater than or Equal to 25 kg) in Accordance with Creatinine Clearance
Creatinine Clearance (mL/min) | Recommended Dosage of EPIVIR
≥50 | 150 mg twice daily or 300 mg once daily
30-49 | 150 mg once daily
15-29 | 150 mg first dose, then 100 mg once daily
5-14 | 150 mg first dose, then 50 mg once daily
<5 | 50 mg first dose, then 25 mg once daily

No additional dosing of EPIVIR is required after routine (4-hour) hemodialysis or peritoneal dialysis.

Although there are insufficient data to recommend a specific dose adjustment of EPIVIR in pediatric patients with renal impairment, a reduction in the dose and/or an increase in the dosing interval should be considered.

3 DOSAGE FORMS AND STRENGTHS

- EPIVIR Scored Tablets

EPIVIR scored tablets contain 150 mg of lamivudine. The tablets are white, diamond-shaped, scored, film-coated tablets debossed with “GX CJ7” on both sides.

- EPIVIR Tablets

EPIVIR tablets contain 300 mg of lamivudine. The tablets are gray, modified diamond-shaped, film-coated, and engraved with “GX EJ7” on one side and plain on the reverse side.

- EPIVIR Oral Solution

EPIVIR oral solution contains 10 mg of lamivudine per 1 mL. The solution is a clear, colorless to pale yellow, strawberry-banana flavored liquid.

4 CONTRAINDICATIONS

EPIVIR is contraindicated in patients with a previous hypersensitivity reaction to lamivudine.

5 WARNINGS AND PRECAUTIONS

5.1 Patients with Hepatitis B Virus Co-Infection

Posttreatment Exacerbations of Hepatitis

Clinical and laboratory evidence of exacerbations of hepatitis have occurred after discontinuation of lamivudine. These exacerbations have been detected primarily by serum ALT elevations in addition to re‑emergence of HBV DNA. Although most events appear to have been self‑limited, fatalities have been reported in some cases. Similar events have been reported from postmarketing experience after changes from lamivudine‑containing HIV‑1 treatment regimens to non‑lamivudine–containing regimens in patients infected with both HIV‑1 and HBV. The causal relationship to discontinuation of lamivudine treatment is unknown. Patients should be closely monitored with both clinical and laboratory follow‑up for at least several months after stopping treatment.

Important Differences among Lamivudine‑Containing Products

EPIVIR tablets and oral solution contain a higher dose of the same active ingredient (lamivudine) than EPIVIR‑HBV tablets and EPIVIR‑HBV oral solution. EPIVIR‑HBV was developed for patients with chronic hepatitis B. The formulation and dosage of lamivudine in EPIVIR‑HBV are not appropriate for patients co-infected with HIV‑1 and HBV. Safety and efficacy of lamivudine have not been established for treatment of chronic hepatitis B in patients co‑infected with HIV‑1 and HBV. If treatment with EPIVIR‑HBV is prescribed for chronic hepatitis B for a patient with unrecognized or untreated HIV-1 infection, rapid emergence of HIV‑1 resistance is likely to result because of the subtherapeutic dose and the inappropriateness of monotherapy HIV‑1 treatment. If a decision is made to administer lamivudine to patients co‑infected with HIV‑1 and HBV, EPIVIR tablets, EPIVIR oral solution, or another product containing the higher dose of lamivudine should be used as part of an appropriate combination regimen.

Emergence of Lamivudine-Resistant HBV

Safety and efficacy of lamivudine have not been established for treatment of chronic hepatitis B in subjects dually infected with HIV-1 and HBV (see full prescribing information for EPIVIR-HBV). Emergence of hepatitis B virus variants associated with resistance to lamivudine has also been reported in HIV-1–infected subjects who have received lamivudine-containing antiretroviral regimens in the presence of concurrent infection with hepatitis B virus.

5.2 Lactic Acidosis and Severe Hepatomegaly with Steatosis

Lactic acidosis and severe hepatomegaly with steatosis, including fatal cases, have been reported with the use of nucleoside analogues, including EPIVIR. A majority of these cases have been in women. Female sex and obesity may be risk factors for the development of lactic acidosis and severe hepatomegaly with steatosis in patients treated with antiretroviral nucleoside analogues. Treatment with EPIVIR should be suspended in any patient who develops clinical or laboratory findings suggestive of lactic acidosis or pronounced hepatotoxicity, which may include hepatomegaly and steatosis even in the absence of marked transaminase elevations.

5.3 Pancreatitis

In pediatric patients with a history of prior antiretroviral nucleoside exposure, a history of pancreatitis, or other significant risk factors for the development of pancreatitis, EPIVIR should be used with caution. Treatment with EPIVIR should be stopped immediately if clinical signs, symptoms, or laboratory abnormalities suggestive of pancreatitis occur [see Adverse Reactions (6.1)].

5.4 Immune Reconstitution Syndrome

Immune reconstitution syndrome has been reported in patients treated with combination antiretroviral therapy, including EPIVIR. During the initial phase of combination antiretroviral treatment, patients whose immune systems respond may develop an inflammatory response to indolent or residual opportunistic infections (such as Mycobacterium avium infection, cytomegalovirus, Pneumocystis jirovecii pneumonia [PCP], or tuberculosis), which may necessitate further evaluation and treatment.

Autoimmune disorders (such as Graves’ disease, polymyositis, and Guillain-Barré syndrome) have also been reported to occur in the setting of immune reconstitution, however, the time to onset is more variable, and can occur many months after initiation of treatment.

5.5 Lower Virologic Suppression Rates and Increased Risk of Viral Resistance with Oral Solution

Pediatric subjects who received EPIVIR oral solution (at weight band-based doses approximating 8 mg per kg per day) concomitantly with other antiretroviral oral solutions at any time in the ARROW trial had lower rates of virologic suppression, lower plasma lamivudine exposure, and developed viral resistance more frequently than those receiving EPIVIR tablets [see Clinical Pharmacology (12.3), Microbiology (12.4), Clinical Studies (14.2)].

EPIVIR scored tablet is the preferred formulation for HIV-1‑infected pediatric patients who weigh at least 14 kg and for whom a solid dosage form is appropriate. An all-tablet regimen should be used when possible to avoid a potential interaction with sorbitol [see Clinical Pharmacology (12.3)]. Consider more frequent monitoring of HIV-1 viral load when treating with EPIVIR oral solution.

6 ADVERSE REACTIONS

The following adverse reactions are discussed in other sections of the labeling:

- Exacerbations of hepatitis B [see Boxed Warning, Warnings and Precautions (5.1)].
- Lactic acidosis and severe hepatomegaly with steatosis [see Warnings and Precautions (5.2)].
- Pancreatitis [see Warnings and Precautions (5.3)].
- Immune reconstitution syndrome [see Warnings and Precautions (5.4)].

6.1 Clinical Trials Experience

Clinical Trials Experience in Adult Subjects

Because clinical trials are conducted under widely varying conditions, adverse reaction rates observed in the clinical trials of a drug cannot be directly compared with rates in the clinical trials of another drug and may not reflect the rates observed in clinical practice.

The safety profile of EPIVIR in adults is primarily based on 3,568 HIV-1–infected subjects in 7 clinical trials.

The most common adverse reactions are headache, nausea, malaise, fatigue, nasal signs and symptoms, diarrhea, and cough.

Selected clinical adverse reactions in greater than or equal to 5% of subjects during therapy with EPIVIR 150 mg twice daily plus RETROVIR 200 mg 3 times daily for up to 24 weeks are listed in Table 3.

Table 3. Selected Clinical Adverse Reactions (Greater than or Equal to 5% Frequency) in Four Controlled Clinical Trials (NUCA3001, NUCA3002, NUCB3001, NUCB3002)
Adverse Reaction | EPIVIR 150 mg; Twice Daily; plus RETROVIR; (n = 251) | RETROVIRa; (n = 230)
Body as a Whole
Headache | 35% | 27%
Malaise & fatigue | 27% | 23%
Fever or chills | 10% | 12%
Digestive
Nausea | 33% | 29%
Diarrhea | 18% | 22%
Nausea & vomiting | 13% | 12%
Anorexia and/or decreased appetite | 10% | 7%
Abdominal pain | 9% | 11%
Abdominal cramps | 6% | 3%
Dyspepsia | 5% | 5%
Nervous System
Neuropathy | 12% | 10%
Insomnia & other sleep disorders | 11% | 7%
Dizziness | 10% | 4%
Depressive disorders | 9% | 4%
Respiratory
Nasal signs & symptoms | 20% | 11%
Cough | 18% | 13%
Skin
Skin rashes | 9% | 6%
Musculoskeletal
Musculoskeletal pain | 12% | 10%
Myalgia | 8% | 6%
Arthralgia | 5% | 5%
a Either zidovudine monotherapy or zidovudine in combination with zalcitabine.

Pancreatitis: Pancreatitis was observed in 9 out of 2,613 adult subjects (0.3%) who received EPIVIR in controlled clinical trials EPV20001, NUCA3001, NUCB3001, NUCA3002, NUCB3002, and NUCB3007 [see Warnings and Precautions (5.3)].

EPIVIR 300 mg Once Daily: The types and frequencies of clinical adverse reactions reported in subjects receiving EPIVIR 300 mg once daily or EPIVIR 150 mg twice daily (in 3-drug combination regimens in EPV20001 and EPV40001) for 48 weeks were similar.

Selected laboratory abnormalities observed during therapy are summarized in Table 4.

Table 4. Frequencies of Selected Grade 3-4 Laboratory Abnormalities in Adults in Four 24-Week Surrogate Endpoint Trials (NUCA3001, NUCA3002, NUCB3001, NUCB3002) and a Clinical Endpoint Trial (NUCB3007)
Test; (Threshold Level) | 24-Week Surrogate Endpoint; Trialsa |  | Clinical Endpoint; Triala
Test; (Threshold Level) | EPIVIR plus RETROVIR | RETROVIRb | EPIVIR; plus; Current Therapyc | Placebo; plus; Current Therapyc
Absolute neutrophil count (<750/mm^3) | 7.2% | 5.4% | 15% | 13%
Hemoglobin (<8.0 g/dL) | 2.9% | 1.8% | 2.2% | 3.4%
Platelets (<50,000/mm^3) | 0.4% | 1.3% | 2.8% | 3.8%
ALT (>5.0 x ULN) | 3.7% | 3.6% | 3.8% | 1.9%
AST (>5.0 x ULN) | 1.7% | 1.8% | 4.0% | 2.1%
Bilirubin (>2.5 x ULN) | 0.8% | 0.4% | ND | ND
Amylase (>2.0 x ULN) | 4.2% | 1.5% | 2.2% | 1.1%
a The median duration on study was 12 months.
b Either zidovudine monotherapy or zidovudine in combination with zalcitabine.
c Current therapy was either zidovudine, zidovudine plus didanosine, or zidovudine plus zalcitabine.
ULN = Upper limit of normal.
ND = Not done.

The frequencies of selected laboratory abnormalities reported in subjects receiving EPIVIR 300 mg once daily or EPIVIR 150 mg twice daily (in 3-drug combination regimens in EPV20001 and EPV40001) were similar.

Clinical Trials Experience in Pediatric Subjects

EPIVIR oral solution has been studied in 638 pediatric subjects aged 3 months to 18 years in 3 clinical trials.

Selected clinical adverse reactions and physical findings with a greater than or equal to 5% frequency during therapy with EPIVIR 4 mg per kg twice daily plus RETROVIR 160 mg per m^2 3 times daily in therapy-naive (less than or equal to 56 days of antiretroviral therapy) pediatric subjects are listed in Table 5.

Table 5. Selected Clinical Adverse Reactions and Physical Findings (Greater than or Equal to 5% Frequency) in Pediatric Subjects in Trial ACTG300
Adverse Reaction | EPIVIR plus RETROVIR; (n = 236) | Didanosine; (n = 235)
Body as a Whole
Fever | 25% | 32%
Digestive
Hepatomegaly | 11% | 11%
Nausea & vomiting | 8% | 7%
Diarrhea | 8% | 6%
Stomatitis | 6% | 12%
Splenomegaly | 5% | 8%
Respiratory
Cough | 15% | 18%
Abnormal breath sounds/wheezing | 7% | 9%
Ear, Nose, and Throat
Signs or symptoms of earsa | 7% | 6%
Nasal discharge or congestion | 8% | 11%
Other
Skin rashes | 12% | 14%
Lymphadenopathy | 9% | 11%
a Includes pain, discharge, erythema, or swelling of an ear.

Pancreatitis: Pancreatitis, which has been fatal in some cases, has been observed in antiretroviral nucleoside‑experienced pediatric subjects receiving EPIVIR alone or in combination with other antiretroviral agents. In an open‑label dose‑escalation trial (NUCA2002), 14 subjects (14%) developed pancreatitis while receiving monotherapy with EPIVIR. Three of these subjects died of complications of pancreatitis. In a second open‑label trial (NUCA2005), 12 subjects (18%) developed pancreatitis. In Trial ACTG300, pancreatitis was not observed in 236 subjects randomized to EPIVIR plus RETROVIR. Pancreatitis was observed in 1 subject in this trial who received open‑label EPIVIR in combination with RETROVIR and ritonavir following discontinuation of didanosine monotherapy [see Warnings and Precautions (5.3)].

Paresthesias and Peripheral Neuropathies: Paresthesias and peripheral neuropathies were reported in 15 subjects (15%) in Trial NUCA2002, 6 subjects (9%) in Trial NUCA2005, and 2 subjects (less than 1%) in Trial ACTG300.

Selected laboratory abnormalities experienced by therapy‑naive (less than or equal to 56 days of antiretroviral therapy) pediatric subjects are listed in Table 6.

Table 6. Frequencies of Selected Grade 3-4 Laboratory Abnormalities in Pediatric Subjects in Trial ACTG300
Test; (Threshold Level) | EPIVIR plus; RETROVIR | Didanosine
Absolute neutrophil count (<400/mm^3) | 8% | 3%
Hemoglobin (<7.0 g/dL) | 4% | 2%
Platelets (<50,000/mm^3) | 1% | 3%
ALT (>10 x ULN) | 1% | 3%
AST (>10 x ULN) | 2% | 4%
Lipase (>2.5 x ULN) | 3% | 3%
Total Amylase (>2.5 x ULN) | 3% | 3%
ULN = Upper limit of normal.

Pediatric Subjects Once-Daily versus Twice-Daily Dosing (COL105677): The safety of once-daily compared with twice-daily dosing of EPIVIR was assessed in the ARROW trial. Primary safety assessment in the ARROW trial was based on Grade 3 and Grade 4 adverse events. The frequency of Grade 3 and 4 adverse events was similar among subjects randomized to once-daily dosing compared with subjects randomized to twice-daily dosing. One event of Grade 4 hepatitis in the once-daily cohort was considered as uncertain causality by the investigator and all other Grade 3 or 4 adverse events were considered not related by the investigator.

Neonates: Limited short-term safety information is available from 2 small, uncontrolled trials in South Africa in neonates receiving lamivudine with or without zidovudine for the first week of life following maternal treatment starting at Week 38 or 36 of gestation [see Clinical Pharmacology (12.3)]. Selected adverse reactions reported in these neonates included increased liver function tests, anemia, diarrhea, electrolyte disturbances, hypoglycemia, jaundice and hepatomegaly, rash, respiratory infections, and sepsis; 3 neonates died (1 from gastroenteritis with acidosis and convulsions, 1 from traumatic injury, and 1 from unknown causes). Two other nonfatal gastroenteritis or diarrhea cases were reported, including 1 with convulsions; 1 infant had transient renal insufficiency associated with dehydration. The absence of control groups limits assessments of causality, but it should be assumed that perinatally exposed infants may be at risk for adverse reactions comparable to those reported in pediatric and adult HIV-1–infected patients treated with lamivudine-containing combination regimens. Long-term effects of in utero and infant lamivudine exposure are not known.

6.2 Postmarketing Experience

The following adverse reactions have been identified during post-approval use of EPIVIR. Because these reactions are reported voluntarily from a population of unknown size, it is not always possible to reliably estimate their frequency or establish a causal relationship to drug exposure. These reactions have been chosen for inclusion due to a combination of their seriousness, frequency of reporting, or potential causal connection to lamivudine.

Body as a Whole

Redistribution/accumulation of body fat.

Endocrine and Metabolic

Hyperglycemia.

General

Weakness.

Hemic and Lymphatic

Anemia (including pure red cell aplasia and severe anemias progressing on therapy).

Hepatic and Pancreatic

Lactic acidosis and hepatic steatosis [see Warnings and Precautions (5.2)], posttreatment exacerbations of hepatitis B [see Warnings and Precautions (5.1)].

Hypersensitivity

Anaphylaxis, urticaria.

Musculoskeletal

Muscle weakness, CPK elevation, rhabdomyolysis.

Skin

Alopecia, pruritus.

7 DRUG INTERACTIONS

7.1 Drugs Inhibiting Organic Cation Transporters

Lamivudine is predominantly eliminated in the urine by active organic cationic secretion. The possibility of interactions with other drugs administered concurrently should be considered, particularly when their main route of elimination is active renal secretion via the organic cationic transport system (e.g., trimethoprim) [see Clinical Pharmacology (12.3)]. No data are available regarding interactions with other drugs that have renal clearance mechanisms similar to that of lamivudine.

7.2 Sorbitol

Coadministration of single doses of lamivudine and sorbitol resulted in a sorbitol dose-dependent reduction in lamivudine exposures. When possible, avoid use of sorbitol-containing medicines with lamivudine [see Warnings and Precautions (5.5), Clinical Pharmacology (12.3)].

8 USE IN SPECIFIC POPULATIONS

8.1 Pregnancy

Pregnancy Exposure Registry

There is a pregnancy exposure registry that monitors pregnancy outcomes in women exposed to EPIVIR during pregnancy. Healthcare providers are encouraged to register patients by calling the Antiretroviral Pregnancy Registry (APR) at 1-800-258-4263.

Risk Summary

Available data from the APR show no difference in the overall risk of birth defects for lamivudine compared with the background rate for birth defects of 2.7% in the Metropolitan Atlanta Congenital Defects Program (MACDP) reference population (see Data). The APR uses the MACDP as the U.S. reference population for birth defects in the general population. The MACDP evaluates women and infants from a limited geographic area and does not include outcomes for births that occurred at less than 20 weeks’ gestation. The rate of miscarriage is not reported in the APR. The estimated background rate of miscarriage in clinically recognized pregnancies in the U.S. general population is 15% to 20%. The background risk for major birth defects and miscarriage for the indicated population is unknown.

In animal reproduction studies, oral administration of lamivudine to pregnant rabbits during organogenesis resulted in embryolethality at systemic exposure (AUC) similar to the recommended clinical dose; however, no adverse development effects were observed with oral administration of lamivudine to pregnant rats during organogenesis at plasma concentrations (Cmax) 35 times the recommended clinical dose (see Data).

Data

Human Data: Based on prospective reports to the APR of over 11,000 exposures to lamivudine during pregnancy resulting in live births (including over 4,500 exposed in the first trimester), there was no difference between the overall risk of birth defects for lamivudine compared with the background birth defect rate of 2.7% in the U.S. reference population of the MACDP. The prevalence of defects in live births was 3.1% (95% CI: 2.6% to 3.6%) following first trimester exposure to lamivudine-containing regimens and 2.8% (95% CI: 2.5% to 3.3%) following second/third trimester exposure to lamivudine-containing regimens.

Lamivudine pharmacokinetics were studied in pregnant women during 2 clinical trials conducted in South Africa. The trials assessed pharmacokinetics in 16 women at 36 weeks’ gestation using 150 mg lamivudine twice daily with zidovudine, 10 women at 38 weeks’ gestation using 150 mg lamivudine twice daily with zidovudine, and 10 women at 38 weeks’ gestation using lamivudine 300 mg twice daily without other antiretrovirals. These trials were not designed or powered to provide efficacy information. Lamivudine concentrations were generally similar in maternal, neonatal, and umbilical cord serum samples. In a subset of subjects, amniotic fluid specimens were collected following natural rupture of membranes and confirmed that lamivudine crosses the placenta in humans. Based on limited data at delivery, median (range) amniotic fluid concentrations of lamivudine were 3.9 (1.2 to 12.8)–fold greater compared with paired maternal serum concentration (n = 8).

Animal Data: Lamivudine was administered orally to pregnant rats (at 90, 600, and 4,000 mg per kg per day) and rabbits (at 90, 300, and 1,000 mg per kg per day and at 15, 40, and 90 mg per kg per day) during organogenesis (on Gestation Days 7 through 16 [rat] and 8 through 20 [rabbit]). No evidence of fetal malformations due to lamivudine was observed in rats and rabbits at doses producing plasma concentrations (Cmax) approximately 35 times higher than human exposure at the recommended daily dose. Evidence of early embryolethality was seen in the rabbit at system exposures (AUC) similar to those observed in humans, but there was no indication of this effect in the rat at plasma concentrations (Cmax) 35 times higher than human exposure at the recommended daily dose. Studies in pregnant rats showed that lamivudine is transferred to the fetus through the placenta. In the fertility/pre-and postnatal development study in rats, lamivudine was administered orally at doses of 180, 900, and 4,000 mg per kg per day (from prior to mating through postnatal Day 20). In the study, development of the offspring, including fertility and reproductive performance, was not affected by maternal administration of lamivudine.

8.2 Lactation

Risk Summary

The Centers for Disease Control and Prevention recommends that HIV-1–infected mothers in the United States not breastfeed their infants to avoid risking postnatal transmission of HIV-1 infection. Lamivudine is present in human milk. There is no information on the effects of lamivudine on the breastfed infant or the effects of the drugs on milk production. Because of the potential for (1) HIV-1 transmission (in HIV-negative infants), (2) developing viral resistance (in HIV-positive infants), and (3) adverse reactions in a breastfed infant, instruct mothers not to breastfeed if they are receiving EPIVIR.

8.4 Pediatric Use

The safety and effectiveness of EPIVIR in combination with other antiretroviral agents have been established in pediatric patients aged 3 months and older. EPIVIR scored tablet is the preferred formulation for HIV-1‑infected pediatric patients who weigh at least 14 kg and for whom a solid dosage form is appropriate because pediatric subjects who received EPIVIR oral solution had lower rates of virologic suppression, lower plasma lamivudine exposure, and developed viral resistance more frequently than those receiving EPIVIR tablets in the ARROW trial [see Dosage and Administration (2.2), Warnings and Precautions (5.5), Adverse Reactions (6.1), Clinical Pharmacology (12.3), Clinical Studies (14.2)].

8.5 Geriatric Use

Clinical trials of EPIVIR did not include sufficient numbers of subjects aged 65 and over to determine whether they respond differently from younger subjects. In general, caution should be exercised in the administration of EPIVIR in elderly patients reflecting the greater frequency of decreased hepatic, renal, or cardiac function, and of concomitant disease or other drug therapy [see Dosage and Administration (2.3), Clinical Pharmacology (12.3)].

8.6 Patients with Impaired Renal Function

Reduction of the dosage of EPIVIR is recommended for patients with impaired renal function [see Dosage and Administration (2.3), Clinical Pharmacology (12.3)].

10 OVERDOSAGE

There is no known specific treatment for overdose with EPIVIR. If overdose occurs, the patient should be monitored and standard supportive treatment applied as required. Because a negligible amount of lamivudine was removed via (4-hour) hemodialysis, continuous ambulatory peritoneal dialysis, and automated peritoneal dialysis, it is not known if continuous hemodialysis would provide clinical benefit in a lamivudine overdose event.

11 DESCRIPTION

EPIVIR (also known as 3TC) is a brand name for lamivudine, a synthetic nucleoside analogue with activity against HIV-1 and HBV. The chemical name of lamivudine is (2R,cis)-4-amino-1-(2-hydroxymethyl-1,3-oxathiolan-5-yl)-(1H)-pyrimidin-2-one. Lamivudine is the (-)enantiomer of a dideoxy analogue of cytidine. Lamivudine has also been referred to as (-)2′,3′-dideoxy, 3′-thiacytidine. It has a molecular formula of C8H11N3O3S and a molecular weight of 229.3 g per mol. It has the following structural formula:

Lamivudine is a white to off-white crystalline solid with a solubility of approximately 70 mg per mL in water at 20°C.

EPIVIR tablets are for oral administration. Each scored 150-mg film-coated tablet contains 150 mg of lamivudine and the inactive ingredients hypromellose, magnesium stearate, microcrystalline cellulose, polyethylene glycol, polysorbate 80, sodium starch glycolate, and titanium dioxide.

Each 300-mg film-coated tablet contains 300 mg of lamivudine and the inactive ingredients black iron oxide, hypromellose, magnesium stearate, microcrystalline cellulose, polyethylene glycol, polysorbate 80, sodium starch glycolate, and titanium dioxide.

EPIVIR oral solution is for oral administration. One milliliter (1 mL) of EPIVIR oral solution contains 10 mg of lamivudine (10 mg per mL) in an aqueous solution and the inactive ingredients artificial strawberry and banana flavors, citric acid (anhydrous), methylparaben, propylene glycol, propylparaben, sodium citrate (dihydrate), and sucrose (200 mg).

12 CLINICAL PHARMACOLOGY

12.1 Mechanism of Action

Lamivudine is an antiretroviral agent [see Microbiology (12.4)].

12.3 Pharmacokinetics

Pharmacokinetics in Adults

The pharmacokinetic properties of lamivudine have been studied in asymptomatic, HIV-1–infected adult subjects after administration of single intravenous (IV) doses ranging from 0.25 to 8 mg per kg, as well as single and multiple (twice-daily regimen) oral doses ranging from 0.25 to 10 mg per kg.

The pharmacokinetic properties of lamivudine have also been studied as single and multiple oral doses ranging from 5 mg to 600 mg per day administered to HBV-infected subjects.

The steady-state pharmacokinetic properties of the EPIVIR 300-mg tablet once daily for 7 days compared with the EPIVIR 150-mg tablet twice daily for 7 days were assessed in a crossover trial in 60 healthy subjects. EPIVIR 300 mg once daily resulted in lamivudine exposures that were similar to EPIVIR 150 mg twice daily with respect to plasma AUC24,ss; however, Cmax,ss was 66% higher and the trough value was 53% lower compared with the 150-mg twice-daily regimen. Intracellular lamivudine triphosphate exposures in peripheral blood mononuclear cells were also similar with respect to AUC24,ss and Cmax24,ss; however, trough values were lower compared with the 150-mg twice-daily regimen. Inter-subject variability was greater for intracellular lamivudine triphosphate concentrations versus lamivudine plasma trough concentrations.

The pharmacokinetics of lamivudine was evaluated in 12 adult HIV-1–infected subjects dosed with lamivudine 150 mg twice daily in combination with other antiretroviral agents. The geometric mean (95% CI) for AUC(0-12) was 5.53 (4.58, 6.67) mcg•h per mL and for Cmax was 1.40 (1.17, 1.69) mcg per mL.

Absorption and Bioavailability: Absolute bioavailability in 12 adult subjects was 86% ± 16% (mean ± SD) for the 150-mg tablet and 87% ± 13% for the oral solution. After oral administration of 2 mg per kg twice a day to 9 adults with HIV-1, the peak serum lamivudine concentration (Cmax) was 1.5 ± 0.5 mcg per mL (mean ± SD). The area under the plasma concentration versus time curve (AUC) and Cmax increased in proportion to oral dose over the range from 0.25 to 10 mg per kg.

The accumulation ratio of lamivudine in HIV-1–positive asymptomatic adults with normal renal function was 1.50 following 15 days of oral administration of 2 mg per kg twice daily.

Effects of Food on Oral Absorption: EPIVIR tablets and oral solution may be administered with or without food. An investigational 25-mg dosage form of lamivudine was administered orally to 12 asymptomatic, HIV-1–infected subjects on 2 occasions, once in the fasted state and once with food (1,099 kcal; 75 grams fat, 34 grams protein, 72 grams carbohydrate). Absorption of lamivudine was slower in the fed state (Tmax: 3.2 ± 1.3 hours) compared with the fasted state (Tmax: 0.9 ± 0.3 hours); Cmax in the fed state was 40% ± 23% (mean ± SD) lower than in the fasted state. There was no significant difference in systemic exposure (AUC∞) in the fed and fasted states.

Distribution: The apparent volume of distribution after IV administration of lamivudine to 20 subjects was 1.3 ± 0.4 L per kg, suggesting that lamivudine distributes into extravascular spaces. Volume of distribution was independent of dose and did not correlate with body weight.

Binding of lamivudine to human plasma proteins is less than 36%. In vitro studies showed that over the concentration range of 0.1 to 100 mcg per mL, the amount of lamivudine associated with erythrocytes ranged from 53% to 57% and was independent of concentration.

Metabolism: Metabolism of lamivudine is a minor route of elimination. In humans, the only known metabolite of lamivudine is the trans-sulfoxide metabolite (approximately 5% of an oral dose after 12 hours). Serum concentrations of this metabolite have not been determined. Lamivudine is not significantly metabolized by cytochrome P450 enzymes.

Elimination: The majority of lamivudine is eliminated unchanged in urine by active organic cationic secretion. In 9 healthy subjects given a single 300-mg oral dose of lamivudine, renal clearance was 199.7 ± 56.9 mL per min (mean ± SD). In 20 HIV-1–infected subjects given a single IV dose, renal clearance was 280.4 ± 75.2 mL per min (mean ± SD), representing 71% ± 16% (mean ± SD) of total clearance of lamivudine.

In most single-dose trials in HIV-1–infected subjects, HBV‑infected subjects, or healthy subjects with serum sampling for 24 hours after dosing, the observed mean elimination half-life (t½) ranged from 5 to 7 hours. In HIV-1–infected subjects, total clearance was 398.5 ± 69.1 mL per min (mean ± SD). Oral clearance and elimination half-life were independent of dose and body weight over an oral dosing range of 0.25 to 10 mg per kg.

Specific Populations

Patients with Renal Impairment: The pharmacokinetic properties of lamivudine have been determined in a small group of HIV-1‑infected adults with impaired renal function (Table 7).

Table 7. Pharmacokinetic Parameters (Mean ± SD) after a Single 300-mg Oral Dose of Lamivudine in 3 Groups of Adults with Varying Degrees of Renal Function
Parameter | Creatinine Clearance Criterion; (Number of Subjects)
Parameter | >60 mL/min; (n = 6) | 10-30 mL/min; (n = 4) | <10 mL/min; (n = 6)
Creatinine clearance (mL/min) | 111 ± 14 | 28 ± 8 | 6 ± 2
Cmax (mcg/mL) | 2.6 ± 0.5 | 3.6 ± 0.8 | 5.8 ± 1.2
AUC∞ (mcg•h/mL) | 11.0 ± 1.7 | 48.0 ± 19 | 157 ± 74
Cl/F (mL/min) | 464 ± 76 | 114 ± 34 | 36 ± 11

Tmax was not significantly affected by renal function. Based on these observations, it is recommended that the dosage of lamivudine be modified in patients with renal impairment [see Dosage and Administration (2.3)].

Based on a trial in otherwise healthy subjects with impaired renal function, hemodialysis increased lamivudine clearance from a mean of 64 to 88 mL per min; however, the length of time of hemodialysis (4 hours) was insufficient to significantly alter mean lamivudine exposure after a single-dose administration. Continuous ambulatory peritoneal dialysis and automated peritoneal dialysis have negligible effects on lamivudine clearance. Therefore, it is recommended, following correction of dose for creatinine clearance, that no additional dose modification be made after routine hemodialysis or peritoneal dialysis.

The effects of renal impairment on lamivudine pharmacokinetics in pediatric patients are not known.

Patients with Hepatic Impairment: The pharmacokinetic properties of lamivudine have been determined in adults with impaired hepatic function. Pharmacokinetic parameters were not altered by diminishing hepatic function. Safety and efficacy of lamivudine have not been established in the presence of decompensated liver disease.

Pregnant Women: Lamivudine pharmacokinetics were studied in 36 pregnant women during 2 clinical trials conducted in South Africa. Lamivudine pharmacokinetics in pregnant women were similar to those seen in non-pregnant adults and in postpartum women. Lamivudine concentrations were generally similar in maternal, neonatal, and umbilical cord serum samples.

Pediatric Patients: The pharmacokinetics of lamivudine have been studied after either single or repeat doses of EPIVIR in 210 pediatric subjects. Pediatric subjects receiving lamivudine oral solution (dosed at approximately 8 mg per kg per day) achieved approximately 25% lower plasma concentrations of lamivudine compared with HIV-1–infected adults. Pediatric subjects receiving lamivudine oral tablets achieved plasma concentrations comparable to or slightly higher than those observed in adults. The absolute bioavailability of both EPIVIR tablets and oral solution are lower in children than adults. The relative bioavailability of EPIVIR oral solution is approximately 40% lower than tablets containing lamivudine in pediatric subjects despite no difference in adults. Lower lamivudine exposures in pediatric patients receiving EPIVIR oral solution is likely due to the interaction between lamivudine and concomitant solutions containing sorbitol (such as ZIAGEN). Modeling of pharmacokinetic data suggests increasing the dosage of EPIVIR oral solution to 5 mg per kg taken orally twice daily or 10 mg per kg taken orally once daily (up to a maximum of 300 mg daily) is needed to achieve sufficient concentrations of lamivudine [see Dosage and Administration (2.2)]. There are no clinical data in HIV-1‑infected pediatric patients coadministered with sorbitol-containing medicines at this dose.

The pharmacokinetics of lamivudine dosed once daily in HIV-1‑infected pediatric subjects aged 3 months through 12 years was evaluated in 3 trials (PENTA-15 [n = 17], PENTA 13 [n = 19], and ARROW PK [n = 35]). All 3 trials were 2-period, crossover, open-label pharmacokinetic trials of twice- versus once-daily dosing of abacavir and lamivudine. These 3 trials demonstrated that once-daily dosing provides similar AUC0-24 to twice-daily dosing of lamivudine at the same total daily dose when comparing the dosing regimens within the same formulation (i.e., either the oral solution or the tablet formulation). The mean Cmax was approximately 80% to 90% higher with lamivudine once-daily dosing compared with twice-daily dosing.

Table 8. Pharmacokinetic Parameters (Geometric Mean [95% CI]) after Repeat Dosing of Lamivudine in 3 Pediatric Trials
 | Trial; (Number of Subjects)
 | ARROW PK; (n = 35) |  | PENTA-13; (n = 19) |  | PENTA-15; (n = 17)a
Age Range | 3-12 years |  | 2-12 years |  | 3-36 months
Formulation | Tablet |  | Solutionb and Tabletc |  | Solutionb
Parameter | Once; Daily | Twice; Daily | Once Daily | Twice; Daily | Once Daily | Twice; Daily
Cmax; (mcg/mL) | 3.17 (2.76, 3.64) | 1.80 (1.59, 2.04) | 2.09 (1.80, 2.42) | 1.11 (0.96, 1.29) | 1.87 (1.65, 2.13) | 1.05 (0.88, 1.26)
AUC(0-24); (mcg•h/mL) | 13.0 (11.4, 14.9) | 12.0 (10.7, 13.4) | 9.80 (8.64, 11.1) | 8.88 (7.67, 10.3) | 8.66 (7.46, 10.1) | 9.48 (7.89, 11.4)
a n = 16 for PENTA-15 Cmax.
b Solution was dosed at 8 mg per kg per day.
c Five subjects in PENTA-13 received lamivudine tablets.

Distribution of lamivudine into cerebrospinal fluid (CSF) was assessed in 38 pediatric subjects after multiple oral dosing with lamivudine. CSF samples were collected between 2 and 4 hours postdose. At the dose of 8 mg per kg per day, CSF lamivudine concentrations in 8 subjects ranged from 5.6% to 30.9% (mean ± SD of 14.2% ± 7.9%) of the concentration in a simultaneous serum sample, with CSF lamivudine concentrations ranging from 0.04 to 0.3 mcg per mL.

Limited, uncontrolled pharmacokinetic and safety data are available from administration of lamivudine (and zidovudine) to 36 infants aged up to 1 week in 2 trials in South Africa. In these trials, lamivudine clearance was substantially reduced in 1-week-old neonates relative to pediatric subjects (aged over 3 months) studied previously. There is insufficient information to establish the time course of changes in clearance between the immediate neonatal period and the age-ranges over 3 months old [see Adverse Reactions (6.1)].

Geriatric Patients: The pharmacokinetics of lamivudine after administration of EPIVIR to subjects over 65 years have not been studied [see Use in Specific Populations (8.5)].

Male and Female Patients: There are no significant or clinically relevant gender differences in lamivudine pharmacokinetics.

Racial Groups: There are no significant or clinically relevant racial differences in lamivudine pharmacokinetics.

Drug Interaction Studies

Effect of Lamivudine on the Pharmacokinetics of Other Agents: Based on in vitro study results, lamivudine at therapeutic drug exposures is not expected to affect the pharmacokinetics of drugs that are substrates of the following transporters: organic anion transporter polypeptide 1B1/3 (OATP1B1/3), breast cancer resistance protein (BCRP), P-glycoprotein (P-gp), multidrug and toxin extrusion protein 1 (MATE)1, MATE2-K, organic cation transporter 1 (OCT)1, OCT2, or OCT3.

Effect of Other Agents on the Pharmacokinetics of Lamivudine: Lamivudine is a substrate of MATE1, MATE2-K, and OCT2 in vitro. Trimethoprim (an inhibitor of these drug transporters) has been shown to increase lamivudine plasma concentrations. This interaction is not considered clinically significant as no dose adjustment of lamivudine is needed.

Lamivudine is a substrate of P-gp and BCRP; however, considering its absolute bioavailability (87%), it is unlikely that these transporters play a significant role in the absorption of lamivudine. Therefore, coadministration of drugs that are inhibitors of these efflux transporters is unlikely to affect the disposition and elimination of lamivudine.

Interferon Alfa: There was no significant pharmacokinetic interaction between lamivudine and interferon alfa in a trial of 19 healthy male subjects.

Ribavirin: In vitro data indicate ribavirin reduces phosphorylation of lamivudine, stavudine, and zidovudine. However, no pharmacokinetic (e.g., plasma concentrations or intracellular triphosphorylated active metabolite concentrations) or pharmacodynamic (e.g., loss of HIV‑1/HCV virologic suppression) interaction was observed when ribavirin and lamivudine (n = 18), stavudine (n = 10), or zidovudine (n = 6) were coadministered as part of a multi‑drug regimen to HIV‑1/HCV co‑infected subjects.

Sorbitol (Excipient): Lamivudine and sorbitol solutions were coadministered to 16 healthy adult subjects in an open-label, randomized-sequence, 4-period, crossover trial. Each subject received a single 300-mg dose of lamivudine oral solution alone or coadministered with a single dose of 3.2 grams, 10.2 grams, or 13.4 grams of sorbitol in solution. Coadministration of lamivudine with sorbitol resulted in dose-dependent decreases of 20%, 39%, and 44% in the AUC(0-24), 14%, 32%, and 36% in the AUC(∞), and 28%, 52%, and 55% in the Cmax; of lamivudine, respectively.

Trimethoprim/Sulfamethoxazole: Lamivudine and TMP/SMX were coadministered to 14 HIV‑1–positive subjects in a single‑center, open‑label, randomized, crossover trial. Each subject received treatment with a single 300‑mg dose of lamivudine and TMP 160 mg/SMX 800 mg once a day for 5 days with concomitant administration of lamivudine 300 mg with the fifth dose in a crossover design. Coadministration of TMP/SMX with lamivudine resulted in an increase of 43% ± 23% (mean ± SD) in lamivudine AUC∞, a decrease of 29% ± 13% in lamivudine oral clearance, and a decrease of 30% ± 36% in lamivudine renal clearance. The pharmacokinetic properties of TMP and SMX were not altered by coadministration with lamivudine. There is no information regarding the effect on lamivudine pharmacokinetics of higher doses of TMP/SMX such as those used in treat PCP.

Zidovudine: No clinically significant alterations in lamivudine or zidovudine pharmacokinetics were observed in 12 asymptomatic HIV-1–infected adult subjects given a single dose of zidovudine (200 mg) in combination with multiple doses of lamivudine (300 mg every 12 hours).

12.4 Microbiology

Mechanism of Action

Lamivudine is a synthetic nucleoside analogue. Intracellularly, lamivudine is phosphorylated to its active 5′-triphosphate metabolite, lamivudine triphosphate (3TC-TP). The principal mode of action of 3TC-TP is inhibition of HIV-1 reverse transcriptase (RT) via DNA chain termination after incorporation of the nucleotide analogue.

Antiviral Activity

The antiviral activity of lamivudine against HIV‑1 was assessed in a number of cell lines including monocytes and fresh human peripheral blood lymphocytes (PBMCs) using standard susceptibility assays. EC50 values were in the range of 0.003 to 15 microM (1 microM = 0.23 mcg per mL). The median EC50 values of lamivudine were 60 nM (range: 20 to 70 nM), 35 nM (range: 30 to 40 nM), 30 nM (range: 20 to 90 nM), 20 nM (range: 3 to 40 nM), 30 nM (range: 1 to 60 nM), 30 nM (range: 20 to 70 nM), 30 nM (range: 3 to 70 nM), and 30 nM (range: 20 to 90 nM) against HIV‑1 clades A-G and group O viruses (n = 3 except n = 2 for clade B) respectively. The EC50 values against HIV‑2 isolates (n = 4) ranged from 0.003 to 0.120 microM in PBMCs. Lamivudine was not antagonistic to all tested anti-HIV agents. Ribavirin (50 microM) used in the treatment of chronic HCV infection decreased the anti-HIV‑1 activity of lamivudine by 3.5‑fold in MT‑4 cells.

Resistance

Lamivudine‑resistant variants of HIV‑1 have been selected in cell culture. Genotypic analysis showed that the resistance was due to a specific amino acid substitution in the HIV‑1 reverse transcriptase at codon 184 changing the methionine to either valine or isoleucine (M184V/I).

HIV‑1 strains resistant to both lamivudine and zidovudine have been isolated from subjects. Susceptibility of clinical isolates to lamivudine and zidovudine was monitored in controlled clinical trials. In subjects receiving lamivudine monotherapy or combination therapy with lamivudine plus zidovudine, HIV‑1 isolates from most subjects became phenotypically and genotypically resistant to lamivudine within 12 weeks.

Genotypic and Phenotypic Analysis of On‑Therapy HIV‑1 Isolates from Subjects with Virologic Failure

Trial EPV20001: Fifty‑three of 554 (10%) subjects enrolled in EPV20001 were identified as virological failures (plasma HIV‑1 RNA level greater than or equal to 400 copies per mL) by Week 48. Twenty-eight subjects were randomized to the lamivudine once‑daily treatment group and 25 to the lamivudine twice‑daily treatment group. The median baseline plasma HIV‑1 RNA levels of subjects in the lamivudine once‑daily group and lamivudine twice‑daily group were 4.9 log10 copies per mL and 4.6 log10 copies per mL, respectively.

Genotypic analysis of on‑therapy isolates from 22 subjects identified as virologic failures in the lamivudine once‑daily group showed that isolates from 8 of 22 subjects contained a treatment‑emergent lamivudine resistance‑associated substitution (M184V or M184I), isolates from 0 of 22 subjects contained treatment‑emergent amino acid substitutions associated with zidovudine resistance (M41L, D67N, K70R, L210W, T215Y/F, or K219Q/E), and isolates from 10 of 22 subjects contained treatment‑emergent amino acid substitutions associated with efavirenz resistance (L100I, K101E, K103N, V108I, or Y181C).

Genotypic analysis of on‑therapy isolates from subjects (n = 22) in the lamivudine twice‑daily treatment group showed that isolates from 5 of 22 subjects contained treatment‑emergent lamivudine resistance substitutions, isolates from 1 of 22 subjects contained treatment‑emergent zidovudine resistance substitutions, and isolates from 7 of 22 subjects contained treatment‑emergent efavirenz resistance substitutions.

Phenotypic analysis of baseline‑matched on‑therapy HIV‑1 isolates from subjects (n = 13) receiving lamivudine once daily showed that isolates from 7 of 13 subjects showed an 85- to 299‑fold decrease in susceptibility to lamivudine, isolates from 12 of 13 subjects were susceptible to zidovudine, and isolates from 8 of 13 subjects exhibited a 25- to 295‑fold decrease in susceptibility to efavirenz.

Phenotypic analysis of baseline‑matched on‑therapy HIV‑1 isolates from subjects (n = 13) receiving lamivudine twice daily showed that isolates from 4 of 13 subjects exhibited a 29- to 159‑fold decrease in susceptibility to lamivudine, isolates from all 13 subjects were susceptible to zidovudine, and isolates from 3 of 13 subjects exhibited a 21- to 342‑fold decrease in susceptibility to efavirenz.

Trial EPV40001: Fifty subjects received lamivudine 300 mg once daily plus zidovudine 300 mg twice daily plus abacavir 300 mg twice daily and 50 subjects received lamivudine 150 mg plus zidovudine 300 mg plus abacavir 300 mg all twice-daily. The median baseline plasma HIV‑1 RNA levels for subjects in the 2 groups were 4.79 log10 copies per mL and 4.83 log10 copies per mL, respectively. Fourteen of 50 subjects in the lamivudine once‑daily treatment group and 9 of 50 subjects in the lamivudine twice‑daily group were identified as virologic failures.

Genotypic analysis of on‑therapy HIV‑1 isolates from subjects (n = 9) in the lamivudine once‑daily treatment group showed that isolates from 6 subjects had an abacavir and/or lamivudine resistance‑associated substitution M184V alone. On‑therapy isolates from subjects (n = 6) receiving lamivudine twice daily showed that isolates from 2 subjects had M184V alone, and isolates from 2 subjects harbored the M184V substitution in combination with zidovudine resistance‑associated amino acid substitutions.

Phenotypic analysis of on‑therapy isolates from subjects (n = 6) receiving lamivudine once daily showed that HIV‑1 isolates from 4 subjects exhibited a 32- to 53‑fold decrease in susceptibility to lamivudine. HIV‑1 isolates from these 6 subjects were susceptible to zidovudine.

Phenotypic analysis of on‑therapy isolates from subjects (n = 4) receiving lamivudine twice daily showed that HIV‑1 isolates from 1 subject exhibited a 45‑fold decrease in susceptibility to lamivudine and a 4.5‑fold decrease in susceptibility to zidovudine.

Pediatrics: Pediatric subjects receiving lamivudine oral solution concomitantly with other antiretroviral oral solutions (abacavir, nevirapine/efavirenz, or zidovudine) in ARROW developed viral resistance more frequently than those receiving tablets. At randomization to once-daily or twice-daily dosing of EPIVIR plus abacavir, 13% of subjects who started on tablets and 32% of subjects who started on solution had resistance substitutions. The resistance profile observed in pediatrics is similar to that observed in adults in terms of the genotypic substitutions detected and relative frequency, with the most commonly detected substitutions at M184 (V or I) [see Clinical Studies (14.2)].

Cross-Resistance

Cross-resistance has been observed among nucleoside reverse transcriptase inhibitors (NRTIs). Lamivudine-resistant HIV-1 mutants were cross-resistant in cell culture to didanosine (ddI). Cross-resistance is also expected with abacavir and emtricitabine as these select M184V substitutions.

13 NONCLINICAL TOXICOLOGY

13.1 Carcinogenesis, Mutagenesis, Impairment of Fertility

Carcinogenesis

Long‑term carcinogenicity studies with lamivudine in mice and rats showed no evidence of carcinogenic potential at exposures up to 10 times (mice) and 58 times (rats) the human exposures at the recommended dose of 300 mg.

Mutagenesis

Lamivudine was mutagenic in an L5178Y mouse lymphoma assay and clastogenic in a cytogenetic assay using cultured human lymphocytes. Lamivudine was not mutagenic in a microbial mutagenicity assay, in an in vitro cell transformation assay, in a rat micronucleus test, in a rat bone marrow cytogenetic assay, and in an assay for unscheduled DNA synthesis in rat liver. Lamivudine showed no evidence of in vivo genotoxic activity in the rat at oral doses of up to 2,000 mg per kg, producing plasma levels of 35 to 45 times those in humans at the recommended dose for HIV‑1 infection.

Impairment of Fertility

In a study of reproductive performance, lamivudine administered to rats at doses up to 4,000 mg per kg per day, producing plasma levels 47 to 70 times those in humans, revealed no evidence of impaired fertility and no effect on the survival, growth, and development to weaning of the offspring.

14 CLINICAL STUDIES

The use of EPIVIR is based on the results of clinical trials in HIV-1–infected subjects in combination regimens with other antiretroviral agents. Information from trials with clinical endpoints or a combination of CD4+ cell counts and HIV-1 RNA measurements is included below as documentation of the contribution of lamivudine to a combination regimen in controlled trials.

14.1 Adult Subjects

Clinical Endpoint Trial

NUCB3007 (CAESAR) was a multicenter, double‑blind, placebo-controlled trial comparing continued current therapy (zidovudine alone [62% of subjects] or zidovudine with didanosine or zalcitabine [38% of subjects]) to the addition of EPIVIR or EPIVIR plus an investigational non-nucleoside reverse transcriptase inhibitor (NNRTI), randomized 1:2:1. A total of 1,816 HIV-1–infected adults with 25 to 250 CD4+ cells per mm^3 (median = 122 cells per mm^3) at baseline were enrolled: median age was 36 years, 87% were male, 84% were nucleoside-experienced, and 16% were therapy-naive. The median duration on trial was 12 months. Results are summarized in Table 9.

Table 9. Number of Subjects (%) with at Least One HIV-1 Disease Progression Event or Death
Endpoint | Current; Therapy; (n = 460) | EPIVIR plus; Current; Therapy; (n = 896) | EPIVIR plus an; NNRTIa plus; Current Therapy; (n = 460)
HIV-1 progression or death | 90 (19.6%) | 86 (9.6%) | 41 (8.9%)
Death | 27 (5.9%) | 23 (2.6%) | 14 (3.0%)
a An investigational non-nucleoside reverse transcriptase inhibitor not approved in the United States.

Surrogate Endpoint Trials

Dual Nucleoside Analogue Trials: Principal clinical trials in the initial development of lamivudine compared lamivudine/zidovudine combinations with zidovudine monotherapy or with zidovudine plus zalcitabine. These trials demonstrated the antiviral effect of lamivudine in a 2-drug combination. More recent uses of lamivudine in treatment of HIV-1 infection incorporate it into multiple-drug regimens containing at least 3 antiretroviral drugs for enhanced viral suppression.

Dose Regimen Comparison Surrogate Endpoint Trials in Therapy-Naive Adults: EPV20001 was a multicenter, double‑blind, controlled trial in which subjects were randomized 1:1 to receive EPIVIR 300 mg once daily or EPIVIR 150 mg twice daily, in combination with zidovudine 300 mg twice daily and efavirenz 600 mg once daily. A total of 554 antiretroviral treatment-naive HIV-1–infected adults enrolled: male (79%), white (50%), median age of 35 years, baseline CD4+ cell counts of 69 to 1,089 cells per mm^3 (median = 362 cells per mm^3), and median baseline plasma HIV-1 RNA of 4.66 log10 copies per mL. Outcomes of treatment through 48 weeks are summarized in Figure 1 and Table 10.

Figure 1. Virologic Response through Week 48, EPV20001a,b (Intent-to-Treat)

a Roche AMPLICOR HIV-1 MONITOR.
b Responders at each visit are subjects who had achieved and maintained HIV-1 RNA less than 400 copies per mL without discontinuation by that visit.

Table 10. Outcomes of Randomized Treatment through 48 Weeks (Intent-to-Treat)
Outcome | EPIVIR 300 mg; Once Daily; plus RETROVIR; plus Efavirenz; (n = 278) | EPIVIR 150 mg; Twice Daily; plus RETROVIR; plus Efavirenz; (n = 276)
Respondera | 67% | 65%
Virologic failureb | 8% | 8%
Discontinued due to clinical progression | <1% | 0%
Discontinued due to adverse events | 6% | 12%
Discontinued due to other reasonsc | 18% | 14%
a Achieved confirmed plasma HIV-1 RNA less than 400 copies per mL and maintained through 48 weeks.
b Achieved suppression but rebounded by Week 48, discontinued due to virologic failure, insufficient viral response according to the investigator, or never suppressed through Week 48.
c Includes consent withdrawn, lost to follow-up, protocol violation, data outside the trial-defined schedule, and randomized but never initiated treatment.

The proportions of subjects with HIV-1 RNA less than 50 copies per mL (via Roche Ultrasensitive assay) through Week 48 were 61% for subjects receiving EPIVIR 300 mg once daily and 63% for subjects receiving EPIVIR 150 mg twice daily. Median increases in CD4+ cell counts were 144 cells per mm^3 at Week 48 in subjects receiving EPIVIR 300 mg once daily and 146 cells per mm^3 for subjects receiving EPIVIR 150 mg twice daily.

A small, randomized, open‑label pilot trial, EPV40001, was conducted in Thailand. A total of 159 treatment‑naive adult subjects (male 32%, Asian 100%, median age 30 years, baseline median CD4+ cell count 380 cells per mm^3, median plasma HIV‑1 RNA 4.8 log10 copies per mL) were enrolled. Two of the treatment arms in this trial provided a comparison between lamivudine 300 mg once daily (n = 54) and lamivudine 150 mg twice daily (n = 52), each in combination with zidovudine 300 mg twice daily and abacavir 300 mg twice daily. In intent‑to‑treat analyses of 48‑week data, the proportions of subjects with HIV‑1 RNA below 400 copies per mL were 61% (33 of 54) in the group randomized to once‑daily lamivudine and 75% (39 of 52) in the group randomized to receive all 3 drugs twice daily; the proportions with HIV‑1 RNA below 50 copies per mL were 54% (29 of 54) in the once‑daily lamivudine group and 67% (35 of 52) in the all‑twice‑daily group; and the median increases in CD4+ cell counts were 166 cells per mm^3 in the once‑daily lamivudine group and 216 cells per mm^3 in the all‑twice‑daily group.

14.2 Pediatric Subjects

Clinical Endpoint Trial

ACTG300 was a multicenter, randomized, double‑blind trial that provided for comparison of EPIVIR plus RETROVIR (zidovudine) with didanosine monotherapy. A total of 471 symptomatic, HIV-1–infected therapy-naive (less than or equal to 56 days of antiretroviral therapy) pediatric subjects were enrolled in these 2 treatment arms. The median age was 2.7 years (range: 6 weeks to 14 years), 58% were female, and 86% were non-white. The mean baseline CD4+ cell count was 868 cells per mm^3 (mean: 1,060 cells per mm^3 and range: 0 to 4,650 cells per mm^3 for subjects aged less than or equal to 5 years; mean: 419 cells per mm^3 and range: 0 to 1,555 cells per mm^3 for subjects aged over 5 years) and the mean baseline plasma HIV-1 RNA was 5.0 log10 copies per mL. The median duration on trial was 10.1 months for the subjects receiving EPIVIR plus RETROVIR and 9.2 months for subjects receiving didanosine monotherapy. Results are summarized in Table 11.

Table 11. Number of Subjects (%) Reaching a Primary Clinical Endpoint (Disease Progression or Death)
Endpoint | EPIVIR plus; RETROVIR; (n = 236) | Didanosine; (n = 235)
HIV-1 disease progression or death (total) | 15 (6.4%) | 37 (15.7%)
Physical growth failure | 7 (3.0%) | 6 (2.6%)
Central nervous system deterioration | 4 (1.7%) | 12 (5.1%)
CDC Clinical Category C | 2 (0.8%) | 8 (3.4%)
Death | 2 (0.8%) | 11 (4.7%)

Once-Daily Dosing

ARROW (COL105677) was a 5-year randomized, multicenter trial which evaluated multiple aspects of clinical management of HIV-1 infection in pediatric subjects. HIV-1–infected, treatment-naïve subjects aged 3 months to 17 years were enrolled and treated with a first-line regimen containing EPIVIR and abacavir, dosed twice daily according to World Health Organization recommendations. After a minimum of 36 weeks on treatment, subjects were given the option to participate in Randomization 3 of the ARROW trial, comparing the safety and efficacy of once-daily dosing with twice-daily dosing of EPIVIR and abacavir, in combination with a third antiretroviral drug, for an additional 96 weeks. Of the 1,206 original ARROW subjects, 669 participated in Randomization 3. Virologic suppression was not a requirement for participation: at baseline for Randomization 3 (following a minimum of 36 weeks of twice-daily treatment), 75% of subjects in the twice-daily cohort were virologically suppressed, compared with 71% of subjects in the once-daily cohort.

The proportion of subjects with HIV-1 RNA of less than 80 copies per mL through 96 weeks is shown in Table 12. The differences between virologic responses in the two treatment arms were comparable across baseline characteristics for gender and age.

Table 12. Virologic Outcome of Randomized Treatment at Week 96a (ARROW Randomization 3)
Outcome | EPIVIR plus; Abacavir; Twice-Daily Dosing; (n = 333) | EPIVIR plus; Abacavir; Once-Daily Dosing; (n = 336)
HIV-1 RNA <80 copies/mLb | 70% | 67%
HIV-1 RNA ≥80 copies/mLc | 28% | 31%
No virologic data
Discontinued due to adverse event or death | 1% | <1%
Discontinued study for other reasonsd | 0% | <1%
Missing data during window but on study | 1% | 1%
a Analyses were based on the last observed viral load data within the Week 96 window.
b Predicted difference (95% CI) of response rate is -4.5% (-11% to 2%) at Week 96.
c Includes subjects who discontinued due to lack or loss of efficacy or for reasons other than an adverse event or death and had a viral load value of greater than or equal to 80 copies per mL, or subjects who had a switch in background regimen that was not permitted by the protocol.
d Other includes reasons such as withdrew consent, loss to follow-up, etc. and the last available HIV-1 RNA less than 80 copies per mL (or missing).

Analyses by formulation demonstrated the proportion of subjects with HIV-1 RNA of less than 80 copies per mL at randomization and Week 96 was higher in subjects who had received tablet formulations of EPIVIR and abacavir (75% [458/610] and 72% [434/601]) than in those who had received solution formulation(s) (with EPIVIR solution given at weight band-based doses approximating 8 mg per kg per day) at any time (52% [29/56] and 54% [30/56]), respectively [see Warnings and Precautions (5.5)]. These differences were observed in each different age group evaluated.

16 HOW SUPPLIED/STORAGE AND HANDLING

EPIVIR scored tablets contain 150 mg of lamivudine, are white, diamond-shaped, film-coated, and debossed with “GX CJ7” on both sides. Packaged as follows:

Bottle of 60 tablets (NDC 49702-203-18) with child-resistant closure.

EPIVIR tablets contain 300 mg of lamivudine, are gray, modified diamond-shaped, film-coated, and engraved with “GX EJ7” on one side and plain on the reverse side. Packaged as follows:

Bottle of 30 tablets (NDC 49702-204-13) with child-resistant closure.

Recommended Storage:

Store EPIVIR tablets at 25°C (77°F); excursions permitted to 15° to 30°C (59° to 86°F) [see USP Controlled Room Temperature].

EPIVIR oral solution is a clear, colorless to pale yellow, strawberry‑banana-flavored liquid. Each mL of the solution contains 10 mg of lamivudine. Packaged as follows:

Plastic bottle of 240 mL (NDC 49702-205-48) with child-resistant closure. This product does not require reconstitution.

Store in tightly closed bottles at 25°C (77°F) [see USP Controlled Room Temperature].

17 PATIENT COUNSELING INFORMATION

Advise the patient to read the FDA-approved patient labeling (Patient Information).

Patients with Hepatitis B or C Co-Infection

Inform patients co‑infected with HIV‑1 and HBV that deterioration of liver disease has occurred in some cases when treatment with lamivudine was discontinued. Advise patients to discuss any changes in regimen with their healthcare provider [see Warnings and Precautions (5.1)].

Differences in Formulations of EPIVIR

Advise patients that EPIVIR tablets and oral solution contain a higher dose of the same active ingredient (lamivudine) as EPIVIR‑HBV tablets and oral solution. If a decision is made to include lamivudine in the HIV‑1 treatment regimen of a patient co‑infected with HIV‑1 and HBV, the formulation and dosage of lamivudine in EPIVIR (not EPIVIR‑HBV) should be used [see Warnings and Precautions (5.1)].

Lactic Acidosis/Hepatomegaly with Steatosis

Advise patients that lactic acidosis and severe hepatomegaly with steatosis have been reported with use of nucleoside analogues and other antiretrovirals. Advise patients to stop taking EPIVIR if they develop clinical symptoms suggestive of lactic acidosis or pronounced hepatotoxicity [see Warnings and Precautions (5.2)].

Risk of Pancreatitis

Advise parents or guardians to monitor pediatric patients for signs and symptoms of pancreatitis [see Warnings and Precautions (5.3)].

Immune Reconstitution Syndrome

Advise patients to inform their healthcare provider immediately of any signs and symptoms of infection as inflammation from previous infection may occur soon after combination antiretroviral therapy, including when EPIVIR is started [see Warnings and Precautions (5.4)].

Lower Virologic Suppression Rates and Increased Risk of Viral Resistance with Oral Solution

Advise patients that an all-tablet regimen should be used when possible due to an increased rate of treatment failure among pediatric subjects who received EPIVIR oral solution concomitantly with other antiretroviral oral solutions [see Warnings and Precautions (5.5)].

Sucrose Content of EPIVIR Oral Solution

Advise diabetic patients that each 15‑mL dose of EPIVIR oral solution contains 3 grams of sucrose (1 mL = 200 mg of sucrose) [see Description (11)].

Pregnancy Registry

Advise patients that there is a pregnancy exposure registry that monitors pregnancy outcomes in women exposed to EPIVIR during pregnancy [see Use in Specific Populations (8.1)].

Lactation

Instruct women with HIV-1 infection not to breastfeed because HIV‑1 can be passed to the baby in the breast milk [see Use in Specific Populations (8.2)].

Missed Dosage

Instruct patients that if they miss a dose of EPIVIR, to take it as soon as they remember. Advise patients not to double their next dose or take more than the prescribed dose [see Dosage and Administration (2)].

EPIVIR, ZIAGEN, and RETROVIR are trademarks owned by or licensed to the ViiV Healthcare group of companies.

EPIVIR-HBV is a trademark owned by or licensed to the GSK group of companies.

Manufactured for:

ViiV Healthcare

Durham, NC 27701

©2024 ViiV Healthcare group of companies or its licensor.

EPV:14PI

PHARMACIST-DETACH HERE AND GIVE INSTRUCTIONS TO PATIENT

_ _ _ _ _ _ _ _ _ _ _ _ _ _ _ _ _ _ _ _ _ _ _ _ _ _ _ _ _ _ _ _ _ _ _ _ _ _ _ _ _ _ __ _ _ _ _ _ _ _ _

PATIENT INFORMATION

EPIVIR (EP-i-veer) EPIVIR (EP-i-veer)

(lamivudine) (lamivudine)

tablets oral solution

What is the most important information I should know about EPIVIR?

EPIVIR can cause serious side effects, including:

- Worsening of hepatitis B virus in people who have HIV-1 infection. If you have HIV-1 (Human Immunodeficiency Virus type 1) and hepatitis B virus (HBV) infection, your HBV may get worse (flare-up) if you stop taking EPIVIR. A “flare-up” is when your HBV infection suddenly returns in a worse way than before. Worsening liver disease can be serious and may lead to death.
  - Do not run out of EPIVIR. Refill your prescription or talk to your healthcare provider before your EPIVIR is all gone.
  - Do not stop EPIVIR without first talking to your healthcare provider.
  - If you stop taking EPIVIR, your healthcare provider will need to check your health often and do blood tests regularly for several months to check your liver.
- Resistant Hepatitis B Virus (HBV). If you have HIV-1 and hepatitis B, the hepatitis B virus can change (mutate) during your treatment with EPIVIR and become harder to treat (resistant).

What is EPIVIR?

EPIVIR is a prescription medicine used together with other antiretroviral medicines to treat HIV-1 infection.

HIV-1 is the virus that causes Acquired Immune Deficiency Syndrome (AIDS).

EPIVIR tablets and oral solution (used to treat HIV-1 infection) contain a higher dose of the same active ingredient (lamivudine) than is in the medicine EPIVIR-HBV tablets and oral solution (used to treat HBV). If you have both HIV-1 and HBV, you should not use EPIVIR-HBV to treat your infections.

The safety and effectiveness of EPIVIR have not been established in children under 3 months of age.

Who should not take EPIVIR?

Do not take EPIVIR if you are allergic to lamivudine or any of the ingredients in EPIVIR. See the end of this Patient Information leaflet for a complete list of ingredients in EPIVIR.

What should I tell my healthcare provider before taking EPIVIR?

Before you take EPIVIR, tell your healthcare provider if you:

- have or have had liver problems, including hepatitis B or C virus infection.
- have kidney problems.
- have diabetes. Each 15-mL dose (150 mg) of EPIVIR oral solution contains 3 grams of sucrose.
- are pregnant or plan to become pregnant. Taking EPIVIR during pregnancy has not been associated with an increased risk of birth defects. Talk to your healthcare provider if you are pregnant or plan to become pregnant.
Pregnancy Registry. There is a pregnancy registry for women who take antiretroviral medicines during pregnancy. The purpose of this registry is to collect information about the health of you and your baby. Talk to your healthcare provider about how you can take part in this registry.
- are breastfeeding or plan to breastfeed. Do not breastfeed if you take EPIVIR.
  - You should not breastfeed if you have HIV-1 because of the risk of passing HIV-1 to your baby.

Tell your healthcare provider about all the medicines you take, including prescription and over-the-counter medicines, vitamins, and herbal supplements.

Some medications interact with EPIVIR. Keep a list of your medicines and show it to your healthcare provider and pharmacist when you get a new medicine. You can ask your healthcare provider or pharmacist for a list of medicines that interact with EPIVIR.

Do not start taking a new medicine without telling your healthcare provider. Your healthcare provider can tell you if it is safe to take EPIVIR with other medicines.

How should I take EPIVIR?

- Take EPIVIR exactly as your healthcare provider tells you to take it.
- If you miss a dose of EPIVIR, take it as soon as you remember. Do not take 2 doses at the same time or take more than what your healthcare provider tells you to take.
- Stay under the care of a healthcare provider during treatment with EPIVIR.
- EPIVIR may be taken with or without food.
- For children 3 months and older, your healthcare provider will prescribe a dose of EPIVIR based on your child’s body weight.
- Tell your healthcare provider if you or your child has trouble swallowing tablets. EPIVIR also comes as a liquid (oral solution).
- Do not run out of EPIVIR. The virus in your blood may increase and the virus may become harder to treat. When your supply starts to run low, get more from your healthcare provider or pharmacy.
- If you take too much EPIVIR, call your healthcare provider or go to the nearest hospital emergency room right away.

What are the possible side effects of EPIVIR?

- EPIVIR can cause serious side effects including:
- See “What is the most important information I should know about EPIVIR?”
- Build-up of an acid in your blood (lactic acidosis). Lactic acidosis can happen in some people who take EPIVIR. Lactic acidosis is a serious medical emergency that can cause death. Call your healthcare provider right away if you get any of the following symptoms that could be signs of lactic acidosis:

○feel very weak or tired
○unusual (not normal) muscle pain
○trouble breathing
○stomach pain with nausea and vomiting

○feel cold, especially in your arms and legs
○feel dizzy or light-headed
○have a fast or irregular heartbeat

- Serious liver problems can happen in people who take EPIVIR. In some cases, these serious liver problems can lead to death. Your liver may become large (hepatomegaly) and you may develop fat in your liver (steatosis). Call your healthcare provider right away if you get any of the following signs or symptoms of liver problems:

○your skin or the white part of your eyes turns yellow (jaundice)
○dark or “tea-colored” urine
○light-colored stools (bowel movements)

○loss of appetite for several days or longer
○nausea
○pain, aching, or tenderness on the right side of your stomach area

You may be more likely to get lactic acidosis or serious liver problems if you are female or very overweight (obese).

- Risk of inflammation of the pancreas (pancreatitis). Children may be at risk for developing pancreatitis during treatment with EPIVIR if they:

○have taken nucleoside analogue medicines in the past

○have a history of pancreatitis
○have other risk factors for pancreatitis

Call your healthcare provider right away if your child develops signs and symptoms of pancreatitis including severe upper stomach-area pain, with or without nausea and vomiting. Your healthcare provider may tell you to stop giving EPIVIR to your child if their symptoms and blood test results show that your child may have pancreatitis.

- Changes in your immune system (Immune Reconstitution Syndrome) can happen when you start taking HIV-1 medicines. Your immune system may get stronger and begin to fight infections that have been hidden in your body for a long time. Tell your healthcare provider right away if you start having new symptoms after you start taking EPIVIR.

The most common side effects of EPIVIR in adults include:

- headache
- nausea
- generally not feeling well
- tiredness

- nasal signs and symptoms
- diarrhea
- cough

The most common side effects of EPIVIR in children include fever and cough.

Tell your healthcare provider if you have any side effect that bothers you or that does not go away.

These are not all the possible side effects of EPIVIR. Call your doctor for medical advice about side effects. You may report side effects to FDA at 1-800-FDA-1088.

How should I store EPIVIR?

- Store EPIVIR tablets and oral solution at room temperature between 68°F to 77°F (20°C to 25°C).
- Keep bottles of EPIVIR oral solution tightly closed.

Keep EPIVIR and all medicines out of the reach of children.

General information about the safe and effective use of EPIVIR.

Medicines are sometimes prescribed for purposes other than those listed in a Patient Information leaflet. Do not use EPIVIR for a condition for which it was not prescribed. Do not give EPIVIR to other people, even if they have the same symptoms that you have. It may harm them.

You can ask your healthcare provider or pharmacist for information about EPIVIR that is written for health professionals.

For more information, go to www.viivhealthcare.com or call 1-877-844-8872.

What are the ingredients in EPIVIR?

Active ingredient: lamivudine

Inactive ingredients:

EPIVIR scored 150-mg film-coated tablets: hypromellose, magnesium stearate, microcrystalline cellulose, polyethylene glycol, polysorbate 80, sodium starch glycolate, and titanium dioxide.

EPIVIR 300-mg film-coated tablets: black iron oxide, hypromellose, magnesium stearate, microcrystalline cellulose, polyethylene glycol, polysorbate 80, sodium starch glycolate, and titanium dioxide.

EPIVIR oral solution: artificial strawberry and banana flavors, citric acid (anhydrous), methylparaben, propylene glycol, propylparaben, sodium citrate (dihydrate), and sucrose (200 mg per mL).

Manufactured for:
ViiV Healthcare
Durham, NC 27701

EPIVIR is a trademark owned by or licensed to the ViiV Healthcare group of companies. EPIVIR-HBV is a trademark owned by or licensed to the GSK group of companies.

©2024 ViiV Healthcare group of companies or its licensor.

EPV:8PIL

This Patient Information has been approved by the U.S. Food and Drug Administration.

Revised: August 2024

PACKAGE LABEL

PRINCIPAL DISPLAY PANEL

NDC 49702-203-18

EPIVIR

(lamivudine)

TABLETS

150 mg

Rx only

60 Tablets

Each scored tablet contains 150 mg of lamivudine.

Do not accept if membrane seal under cap is missing or broken.

See prescribing information for dosage information.

Store at 25oC (77oF); excursions permitted to 15o to 30oC (59o to 86oF) [see USP Controlled Room Temperature].

Manufactured for:

ViiV Healthcare

Durham, NC 27701

Made in India and Singapore

Trademarks are owned by or licensed to the ViiV Healthcare group of companies.

©2024 ViiV Healthcare group of companies or its licensor.

A095896 (62000000095896) Rev. 09/24

PACKAGE LABEL

PRINCIPAL DISPLAY PANEL

NDC 49702-204-13

EPIVIR

(lamivudine)

TABLETS

300 mg

Rx only

30 Tablets

Each tablet contains 300 mg of lamivudine.

Do not accept if membrane seal under cap is missing or broken.

See prescribing information for dosage information.

Store at 25oC (77oF); excursions permitted to 15o to 30oC (59o to 86oF) [see USP Controlled Room Temperature].

Manufactured for:

ViiV Healthcare

Durham, NC 27701

Made in India and Singapore

Trademarks are owned by or licensed to the ViiV Healthcare group of companies.

©2024 ViiV Healthcare group of companies or its licensor.

A095897 (62000000095897) Rev. 09/24

PACKAGE LABEL

PRINCIPAL DISPLAY PANEL

NDC 49702-205-48

EPIVIR

(lamivudine)

ORAL SOLUTION

10 mg/mL

ViiV Healthcare

ALCOHOL FREE

Rx only

240 mL

Made in India and Singapore

Do not accept if security seal is missing or broken.

©2024 ViiV Healthcare group of companies or its licensor.
30000000001587 Rev. 9/24